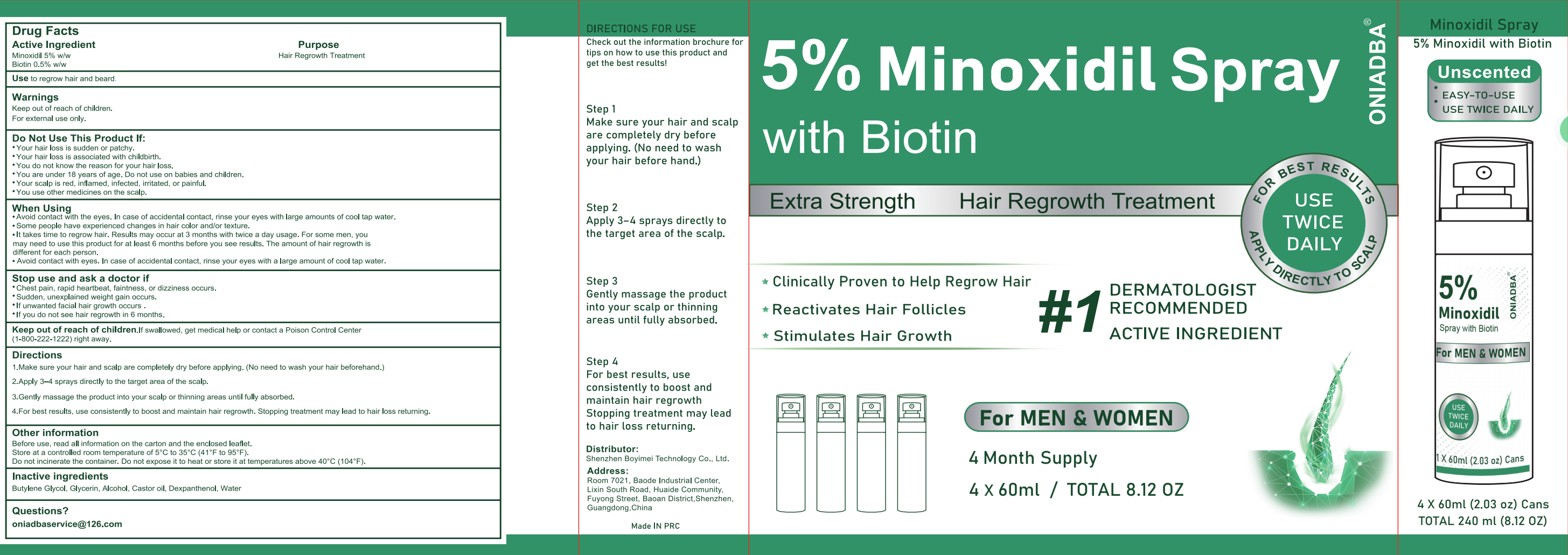 DRUG LABEL: ONIADBA 5% Minoxidil Hair Growth Sprays Serum
NDC: 85992-001 | Form: LIQUID
Manufacturer: Shenzhen Boyimei Technology Co., Ltd.
Category: otc | Type: HUMAN OTC DRUG LABEL
Date: 20250710

ACTIVE INGREDIENTS: MINOXIDIL 0.05 g/1 mL; BIOTIN 0.005 g/1 mL
INACTIVE INGREDIENTS: BUTYLENE GLYCOL; DEXPANTHENOL; CASTOR OIL; ALCOHOL; WATER; GLYCERIN

85992-001 ONIADBA 5% Minoxidil Hair Growth Sprays Serum

ACTIVE INGREDIENT

Minoxidil 5%
Biotin 0.5%

PURPOSE

Hair Regrowth Treatment

INDICATIONS AND USAGE

Use to regrow hair and beard

Keep out of reach of children.
For external use only.

DO NOT USE

Your hair loss is sudden or patchy.
Your hair loss is associated with childbirth.
You do not know the reason for your hair loss.
You are under 18 years of age. Do not use on babies and children.
Your scalp is red, inflamed, infected, irritated, or painful.
You use other medicines on the scalp.

WHEN USING

Avoid contact with the eyes. In case of accidental contact, rinse your eyes with large amounts of cool tap water.
Some people have experienced changes in hair color and/or texture.
lt takes time to regrow hair. Results may occur at 3 months with twice a day usage. For some men, you may need to use this product for at least 6 months before you see results. The amount of hair regrowth is different for each person.
Avoid contact with eyes. In case of accidental contact, rinse your eyes with a large amount of cool tap water.

STOP USE

Chest pain, rapid heartbeat, faintness, or dizziness occurs.
Sudden, unexplained weight gain occurs.
If unwanted facial hair growth occurs .
If you do not see hair regrowth in 6 months.

Keep out of reach of children.lf swallowed, get medical help or contact a Poison Control Center
(1-800-222-1222)right away.

DOSAGE AND ADMINISTRATION

1.Make sure your hair and scalp are completely dry before applying. (No need to wash your hair beforehand.)
2.Apply 3-4 sprays directly to the target area of the scalp.
3.Gently massage the product into your scalp or thinning areas until fully absorbed.
4.For best results, use consistenlly to boost and maintain hair regrowth, Stopping treatment may lead to hair loss returning.

INACTIVE INGREDIENT

Butylene Glycol, Glycerin, Alcohol, Castor oil, Dexpanthenol, Water